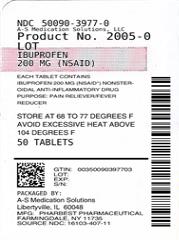 DRUG LABEL: Ibuprofen
NDC: 50090-3977 | Form: TABLET, FILM COATED
Manufacturer: A-S Medication Solutions
Category: otc | Type: HUMAN OTC DRUG LABEL
Date: 20190930

ACTIVE INGREDIENTS: IBUPROFEN 200 mg/1 1
INACTIVE INGREDIENTS: CARNAUBA WAX; SILICON DIOXIDE; STARCH, CORN; HYPROMELLOSE, UNSPECIFIED; ANHYDROUS LACTOSE; MAGNESIUM STEARATE; MICROCRYSTALLINE CELLULOSE; POLYDEXTROSE; POLYETHYLENE GLYCOL, UNSPECIFIED; FERRIC OXIDE RED; STEARIC ACID; SODIUM STARCH GLYCOLATE TYPE A POTATO; TITANIUM DIOXIDE

Drug Facts

Active ingredient (in each tablet)

Ibuprofen 200 mg (NSAID)*
*nonsteroidal anti- inflammatory drug

Purpose

Pain Reliever/ Fever Reducer

Uses

- temporarily relieves minor aches and pain due to:
- headache
- toothache
- backache
- menstrual cramps
- the common cold
- muscular aches
- minor pain of arthritis
- temporarily reduces fever

Warnings

Allergy alert: Ibuprofen may cause a severe allergic reaction, especially in people allergic to Aspirin. Symptoms may include

- hives
- facial swelling
- asthma (wheezing)
- shock
- skin reddening
- rash
- blisters

If an allergic reaction occurs, stop use and seek medical help right away.
Stomach bleeding warning: This product contains an NSAID, which may cause severe stomach bleeding. The chance is higher if you

- are age 60 or older
- have had stomach ulcers or bleeding problems
- take a blood-thinning (anticoagulant) or steroid drug
- take other drugs containing prescription or nonprescription NSAIDs (aspirin, ibuprofen, naproxen, or others)
- have 3 or more alcoholic drinks every day while using this product
- take more or for a longer time than directed

Do not use

- if you have ever had an allergic reaction to any other pain reliever/ fever reducer
- right before or after heart surgery

Ask a doctor before use if

- stomach bleeding warning applies to you
- you have problems or serious side effects from taking pain relievers or fever reducers
- you have a history of stomach problems, such as heartburn
- you have high blood pressure, heart disease, liver cirrhosis, kidney disease, or asthma
- you are taking a diuretic

Ask a doctor or pharmacist before use if you are

- under a doctor's care for any serious condition
- taking aspirin for heart attack or stroke, because ibuprofen may decrease this benefit of aspirin
- taking any other drug

when using this product

- take with food or milk if stomach upset occurs
- the risk of heart attack or stroke may increase if you use more than directed or for longer than directed

stop use and ask a doctor if

you experience any of the following signs of stomach bleeding:

- feel faint
- vomit blood
- have bloody or black stools
- have stomach pain that does not get better
- pain gets worse or lasts more than 10 days
- fever gets worse or lasts more than 3 days
- redness or swelling is present in the painful area
- any new symptoms appear

If pregnant or breast-feeding,

ask a health professional before use. It is especially important not to use ibuprofen during the last 3 months of pregnancy unless definitely directed to do so by a doctor because it may cause problems in the unborn child or complications during delivery.

Keep out of reach of children.

In case of overdose, get medical help or contact a Poison Control Center right away (1-800-222-1222).

Directions

- Do not take more than directed
- The smallest effective dose should be used

adults and children 12 years of age and over | Take 1 tablet every 4 to 6 hours while symptoms persist. If pain or fever does not respond to 1 tablet, 2 tablets may be used. Do not exceed 6 tablets in 24 hours unless directed by a doctor
children under 12 years | consult a doctor

Other information

- Tamper Evident: do not use if safety seal under cap is broken or missing
- store at room temperature (20o- 25oC)
- avoid excessive heat above 40oC (104oF)

Inactive ingredients

carnuba wax, colloidal silicon dioxide, corn starch, hypromellose, lactose anhydrous, magnesium stearate, microcrystalline cellulose, polydextrose, polyethylene glycol, red iron oxide, stearic acid, sodium starch glycolate, titanium dioxide

Questions or comments?

(866) 562-2756 Mon-Fri: 8 AM to 4 PM

HOW SUPPLIED

Product: 50090-3977

NDC: 50090-3977-0 50 TABLET, FILM COATED in a BOTTLE

NDC: 50090-3977-3 24 TABLET, FILM COATED in a BOTTLE

NDC: 50090-3977-5 30 TABLET, FILM COATED in a BOTTLE

NDC: 50090-3977-6 28 TABLET, FILM COATED in a BOTTLE

NDC: 50090-3977-7 60 TABLET, FILM COATED in a BOTTLE

NDC: 50090-3977-8 100 TABLET, FILM COATED in a BOTTLE

NDC: 50090-3977-2 20 TABLET, FILM COATED in a BOTTLE